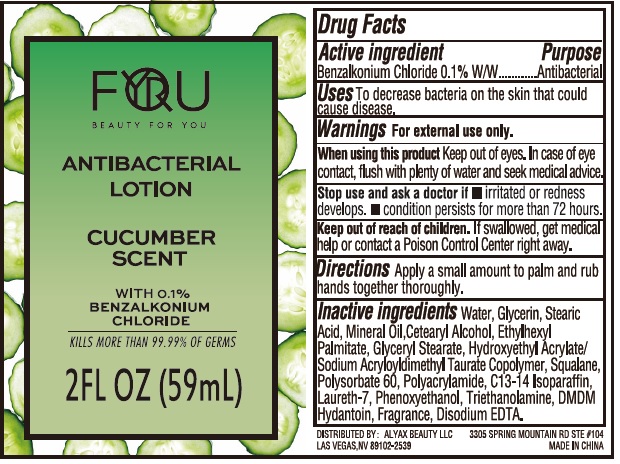 DRUG LABEL: Antibacterial Hand Sanitizer cucumber scent
NDC: 74149-034 | Form: LOTION
Manufacturer: Yiwu Yangjie Daily Chemicals Co.,Ltd.
Category: otc | Type: HUMAN OTC DRUG LABEL
Date: 20200828

ACTIVE INGREDIENTS: BENZALKONIUM CHLORIDE 1.0 mg/1 mL
INACTIVE INGREDIENTS: WATER; GLYCERIN; ETHYLHEXYL PALMITATE; GLYCERYL MONOSTEARATE; CETOSTEARYL ALCOHOL; 2-HYDROXYETHYL ACRYLATE; SQUALANE; POLYSORBATE 60; C13-14 ISOPARAFFIN; LAURETH-7; PHENOXYETHANOL; TROLAMINE; EDETATE DISODIUM

Drug facts

Active ingredient BENZALKONIUM CHLORIDE ........... 0.1 w/w

PURPOSE

Antibacterial

USE

To decrease bacteria on the skin that could cause disease.

KEEP OUT OF REACH OF CHILDREN

If swallowed, get medical help or contact a poison control center right away.

WARNINGS

For external use only

When using this product

- Keep out of eyes. In case of contact flush eyes with water, and seek medical advise.

Stop use and ask a doctor

- If irritation or redness develops.
- condition persists for more than 72 hours.

DOSAGE AND ADMINISTRATION

Apply a small amount to palm and rub hands together thoroughly.

INACTIVE INGREDIENT

Water, Glycerin, Stearic Acid, Mineral Oil, Cetaryl Alcohol, Ethylhexyl Palmltate, Glyceryl Stearate, Hydroxyethyl Acrylate/Sodium Acryloyldimethyl Taurate Copolymer, Squalane, Polysorbate 60, Polyacrylamide, C13-14 Isoparaffin, Laureth-7, Phenoxyethanol, Triethanolamine, DMDM Hydantoin, Fragrance, Disodium EDTA.